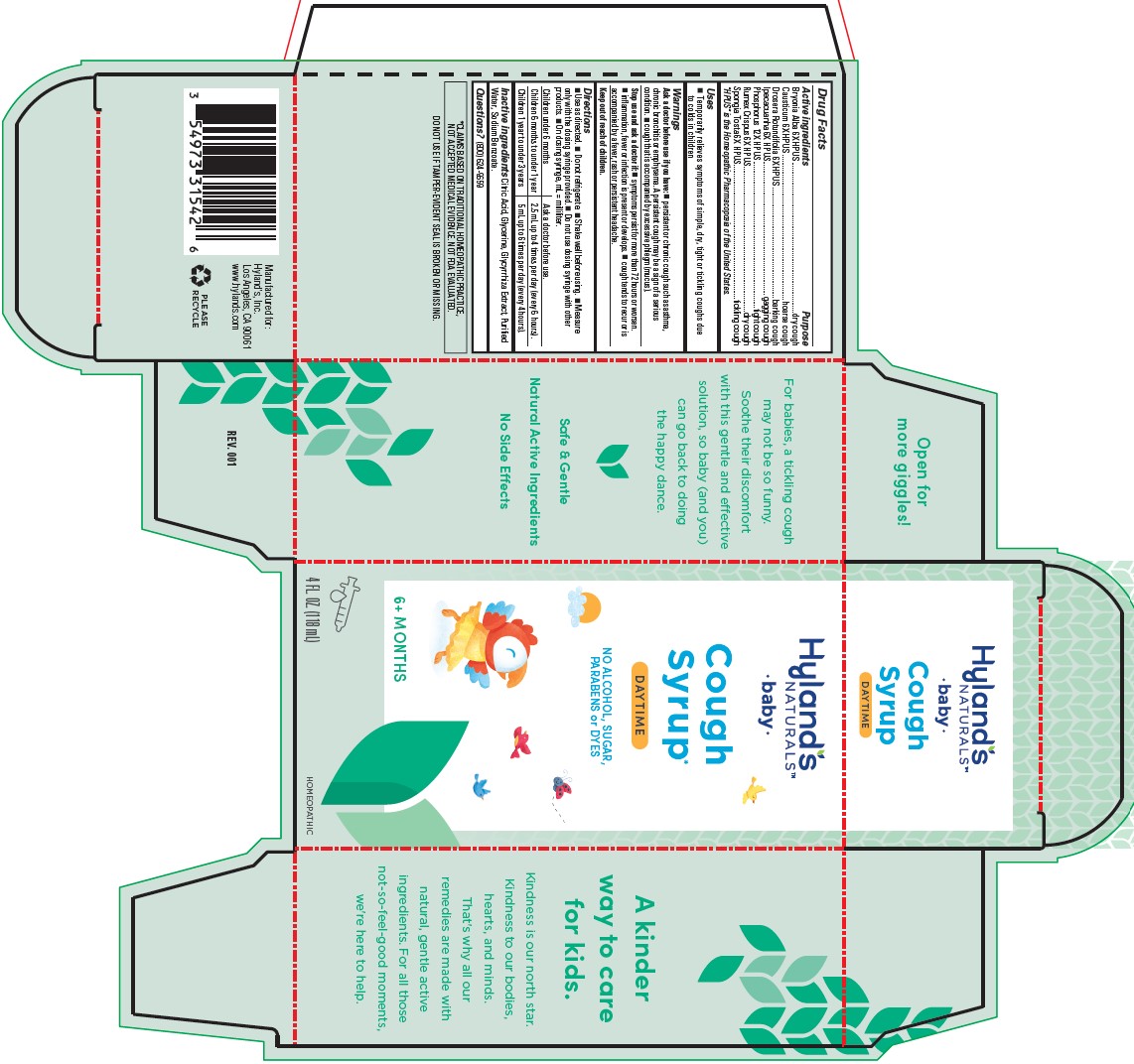 DRUG LABEL: COUGH BABY
NDC: 54973-3154 | Form: SYRUP
Manufacturer: Hyland's Inc.
Category: homeopathic | Type: HUMAN OTC DRUG LABEL
Date: 20251219

ACTIVE INGREDIENTS: IPECAC 6 [hp_X]/1 mL; BRYONIA ALBA ROOT 6 [hp_X]/1 mL; SPONGIA OFFICINALIS SKELETON, ROASTED 6 [hp_X]/1 mL; PHOSPHORUS 12 [hp_X]/1 mL; CAUSTICUM 6 [hp_X]/1 mL; DROSERA ROTUNDIFOLIA 6 [hp_X]/1 mL; RUMEX CRISPUS ROOT 6 [hp_X]/1 mL
INACTIVE INGREDIENTS: LICORICE; WATER; SODIUM BENZOATE; GLYCERIN; CITRIC ACID MONOHYDRATE

Hyland's Naturals Baby Cough Syrup Daytime

PURPOSE

Relieves coughs in babies

Drug Facts

Active ingredients | Purpose
Bryonia Alba 6X HPUS | dry cough
Causticum 6X HPUS | hoarse cough
Drosera Rotundifolia 6X HPUS | barking cough
Ipecacuanha 6X | gagging cough
Phosphorus 12X HPUS | tight cough
Rumex Crispus 6X HPUS | dry cough
Spongia Tosta 6X HPUS | tickling cough

"HPUS" indicates that the active ingredients are in the official Homeopathic

Pharmacopoeia of the United States.

Uses

■ Temporarily relieves the symptoms of simple, dry, tight or tickling coughs due to colds in children.

Warnings

Ask a doctor before use if you have:

■ persistent or chronic cough such as asthma, chronic bronchitis or emphysema. A persistent cough may be a sign of a serious condition. ■ cough that is accompanied by excessive phlegm (mucus).

Stop use and ask a doctor if:

■ symptoms persist for more than 72 hours or worsen. ■ inflammation, fever or infection is present or develops. ■ cough tends to recur or is accompanied by a fever, rash or persistent headache.

Keep out of reach of children.

Keep this and all medications out of the reach of children.

Directions

■ Use as directed. ■ Do not refrigerate. ■ Shake well before using.  Measure
only with the dosing syringe provided. ■ Do not use dosing syringe with other
products. ■ On dosing syringe, mL = milliliter.

Children under 6 months | Ask a doctor before use.
Children 6 months to under 1 year | 2.5 mL up to 4 times per day (every 6 hours).
Children 1 year to under 3 years | 5 mL up to 6 times per day (every 4 hours).

Inactive ingredients

Citric Acid, Glycerine, Glycyrrhiza Extract, Purified Water, Sodium Benzoate.

Questions?

(800) 624-9659

Indications and Usage Uses

Added bullet ■

Dosage and Administration

Directions

updated to

■Shake well before using.

■Measure only with the dosing syringe provided.

■Do not use dosing syringe with other products.

■On dosing syringe, mL = milliliter.

Children under; 6 months | Consult a physician.
Children 6 months; to under 1 year | 2.5 mL up to 4 times per day (every 6 hours).
Children 1 year; to 3 years | 5 mL up to 6 times per day (every 4 hours).

PACKAGE LABEL-118 mL BOTTLE CARTON

Hyland's

NATURALS™

•baby•

Cough

Syrup*

DAYTIME

NO ALCOHOL, SUGAR,

PARABENS or DYES

6+ MONTHS

4 FL. OZ. (118 mL)

HOMEOPATHIC